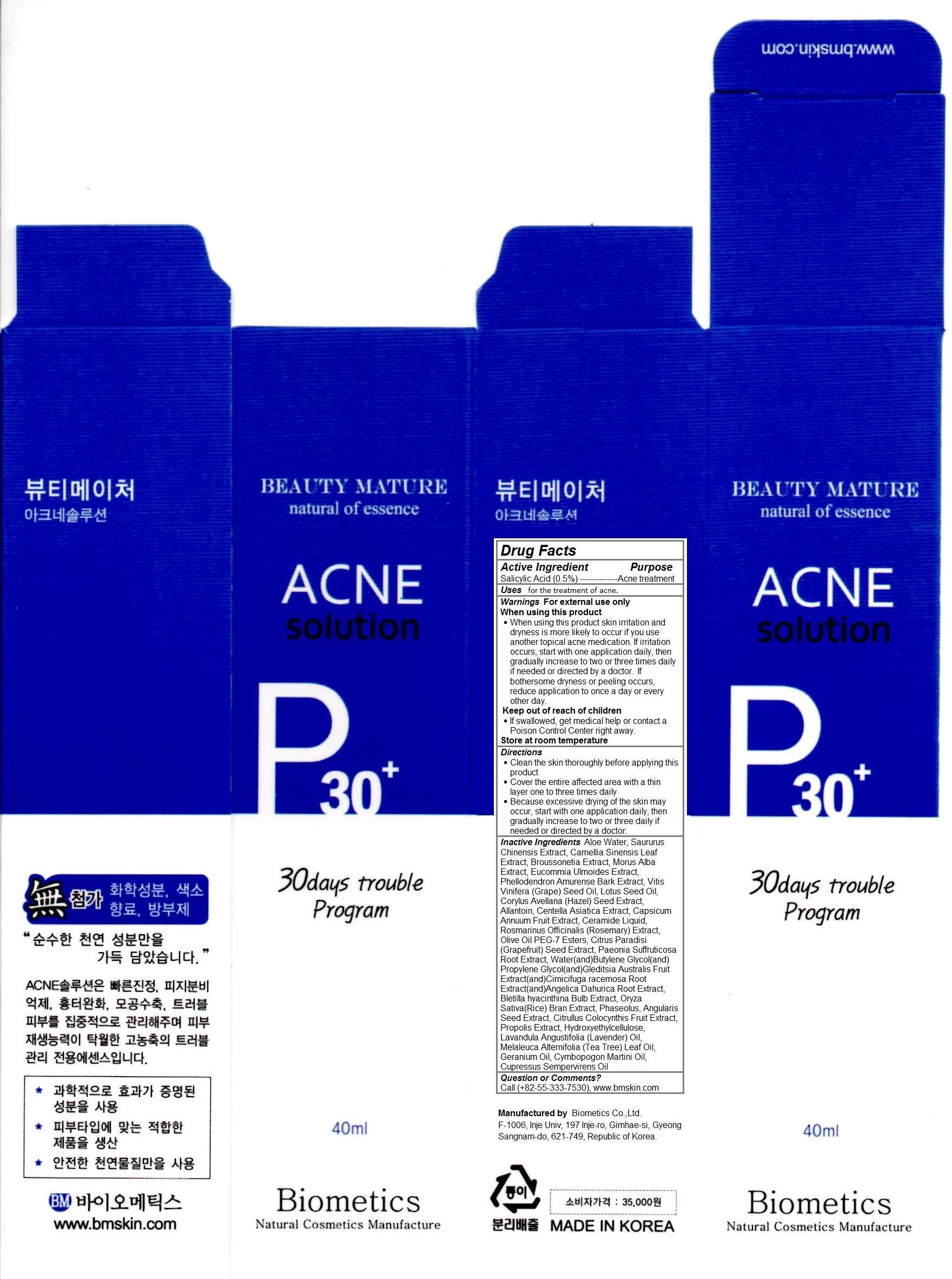 DRUG LABEL: Acne Solution
NDC: 62818-101 | Form: SOLUTION
Manufacturer: Biometics Co.,Ltd.
Category: otc | Type: HUMAN OTC DRUG LABEL
Date: 20140416

ACTIVE INGREDIENTS: salicylic acid 0.2 g/40 g
INACTIVE INGREDIENTS: water; SAURURUS CHINENSIS WHOLE; CAMELLIA SINENSIS WHOLE; BROUSSONETIA PAPYRIFERA WHOLE; MORUS ALBA WHOLE; EUCOMMIA ULMOIDES WHOLE; PHELLODENDRON AMURENSE BARK; VITIS VINIFERA SEED; LOTUS CORNICULATUS FLOWER VOLATILE OIL; CORYLUS AVELLANA POLLEN EXTRACT; ALLANTOIN; CENTELLA ASIATICA; CAPSICUM ANNUUM WHOLE; ROSMARINUS OFFICINALIS WHOLE; OLIVE OIL; CITRUS PARADISI SEED; PAEONIA SUFFRUTICOSA ROOT; PROPOLIS WAX; CETYL HYDROXYETHYLCELLULOSE (350000 MW); LAVANDULA ANGUSTIFOLIA WHOLE; MELALEUCA ALTERNIFOLIA LEAF; GERANIUM OIL, ALGERIAN TYPE; CYMBOPOGON MARTINI WHOLE; CUPRESSUS SEMPERVIRENS LEAF OIL

Acne Solution